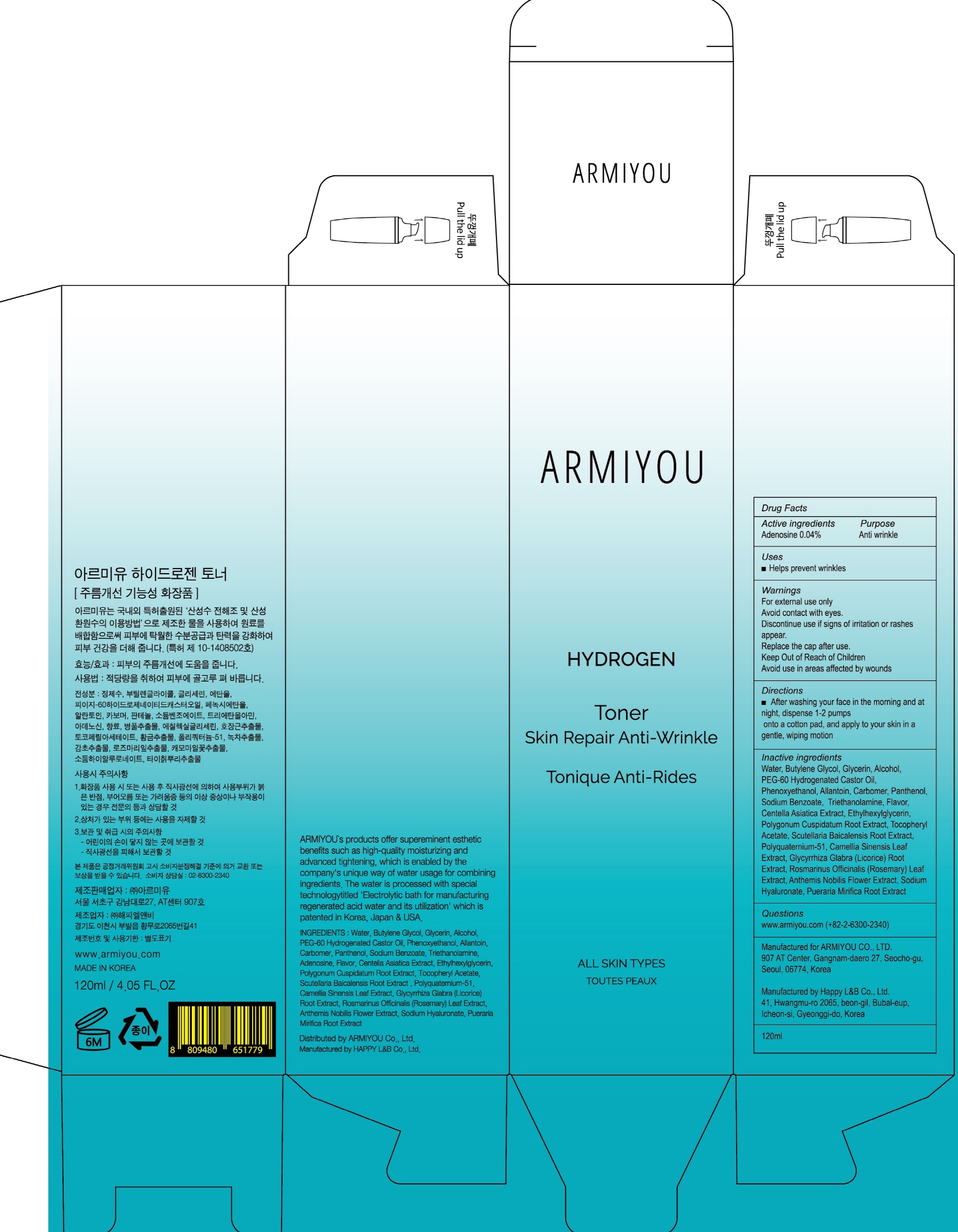 DRUG LABEL: ARMIYOU HYDROGEN TONER
NDC: 71878-010 | Form: LIQUID
Manufacturer: Armiyou
Category: otc | Type: HUMAN OTC DRUG LABEL
Date: 20171122

ACTIVE INGREDIENTS: Adenosine 0.04 g/120 mL
INACTIVE INGREDIENTS: Water; Butylene Glycol

ACTIVE INGREDIENT

Active ingredients: Adenosine 0.04%

INACTIVE INGREDIENT

Inactive ingredients: Water, Butylene Glycol, Glycerin, Alcohol, PEG-60 Hydrogenated Castor Oil, Phenoxyethanol, Allantoin, Carbomer, Panthenol, Sodium Benzoate, Triethanolamine, Flavor, Centella Asiatica Extract, Ethylhexylglycerin, Polygonum Cuspidatum Root Extract, Tocopheryl Acetate, Scutellaria Baicalensis Root Extract, Polyquaternium-51, Camellia Sinensis Leaf Extract, Glycyrrhiza Glabra (Licorice) Root Extract, Rosmarinus Officinalis (Rosemary) Leaf Extract, Anthemis Nobilis Flower Extract, Sodium Hyaluronate, Pueraria Mirifica Root Extract

PURPOSE

Purpose: Anti wrinkle

WARNINGS

Warnings: For external use only Avoid contact with eyes. Discontinue use if signs of irritation or rashes appear. Replace the cap after use. Keep Out of Reach of Children. Avoid use in areas affected by wounds.

KEEP OUT OF REACH OF CHILDREN

Uses

Uses: Helps prevent wrinkles

Directions

Directions: After washing your face in the morning and at night, dispense 1-2 pumps onto a cotton pad, and apply to your skin in a gentle, wiping motion.